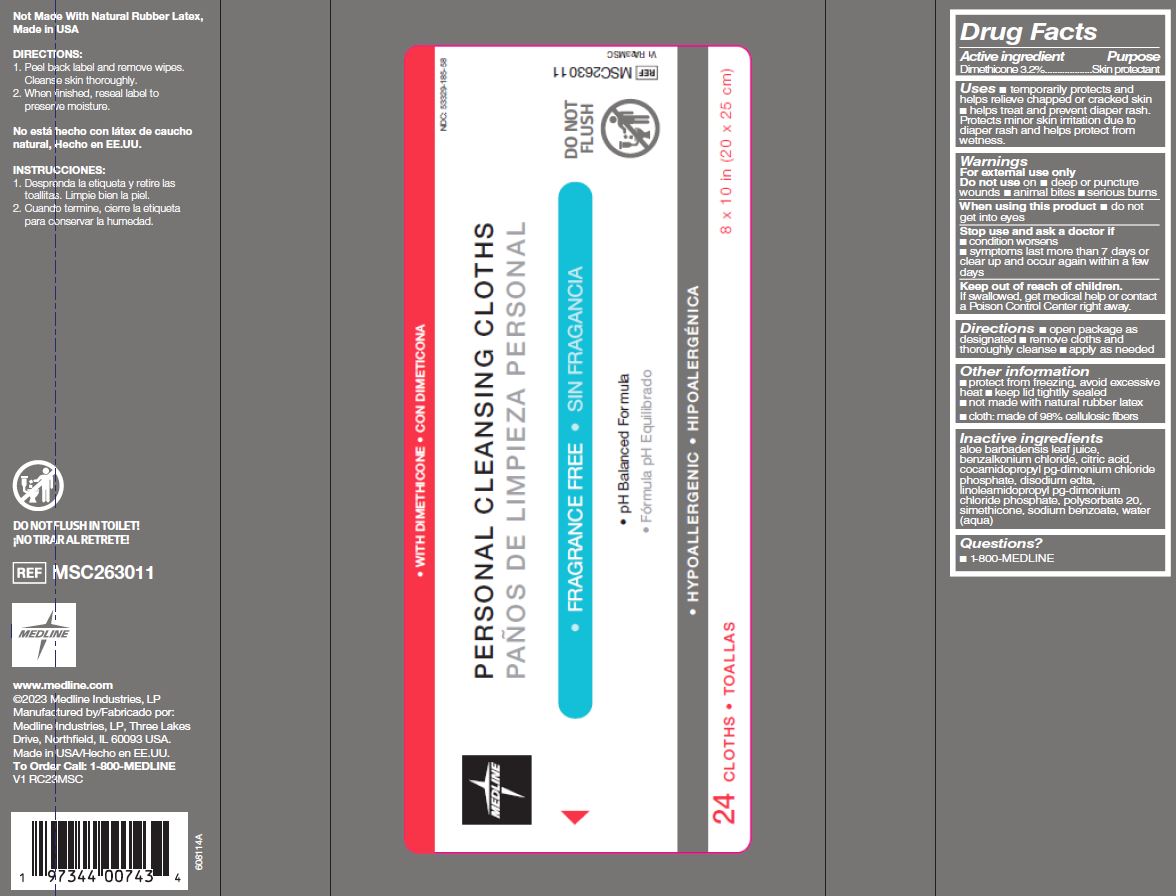 DRUG LABEL: Medline
NDC: 53329-185 | Form: CLOTH
Manufacturer: Medline Industries, LP
Category: otc | Type: HUMAN OTC DRUG LABEL
Date: 20240119

ACTIVE INGREDIENTS: DIMETHICONE 32 mg/1 mL
INACTIVE INGREDIENTS: COCAMIDOPROPYL PG-DIMONIUM CHLORIDE PHOSPHATE; POLYSORBATE 20; EDETATE DISODIUM ANHYDROUS; ALOE VERA LEAF; SILICON DIOXIDE; SODIUM BENZOATE; WATER; BENZALKONIUM CHLORIDE; LINOLEAMIDOPROPYL PROPYLENE GLYCOL-DIMONIUM CHLORIDE PHOSPHATE; CITRIC ACID MONOHYDRATE

185 ReadyFlush Protect Personal Cleansing Cloths (no flushable labeling)

Active ingredient

Dimethicone 3.2 w/v

Purpose

Skin protectant

Uses

- temporarily protects and helps relieve chapped or cracked skin
- helps treat and prevent diaper rash. Protects minor skin irritation due to diaper rash and helps protect from wetness

Warnings

For external use only.

Do not use on

- deep or puncture wounds
- animal bites
- serious burns

When using this product

- do not get into eyes

Stop use and ask a doctor if

- condition worsens
- symptoms last more than 7 days or clear up and occur again within a few days

Keep out of reach of children.

If swallowed, get medical help or contact a Poison Control Center right away.

Directions

- open package as designated
- remove cloths and throughly cleanse
- apply as needed
- for diaper rash: change wet and soiled diapers promptly, cleanse the diaper area, and allow to dry. Apply product liberally as often as necessary, with each diaper change, especially at bedtime or anytime when exposure to wet diapers may be prolonged

Other information

- protect from freezing, avoid excessive heat
- keep lid tightly sealed
- not made with natural rubber latex
- cloth: made of 98% cellulosic fibers

Inactive ingredients

aloe barbadensis leaf juice, benzalkonium chloride, citric acid, cocamidopropyl pg-dimonium chloride phosphate, disodium edta, linoleamidopropyl pg-dimonium chloride phosphate, polysorbate 20， simethicone, sodium benzoate, water (aqua)

Manufacturing Information

Manufactured by:
Medline Industries, LP

Three Lakes Drive, Northfield, IL 60093 USA

Made in USA

www.medline.com

1-800-MEDLINE (633-5463)

REF:MSC263011

V1 RC23MSC